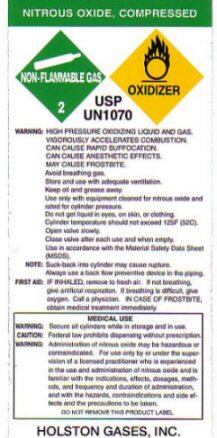 DRUG LABEL: NITROUS OXIDE
NDC: 55050-0008 | Form: GAS
Manufacturer: Holston Gases, Inc
Category: prescription | Type: HUMAN PRESCRIPTION DRUG LABEL
Date: 20100101

ACTIVE INGREDIENTS: NITROUS OXIDE 99 kg/100 kg

NITROUS OXIDE COMPRESSED LABEL

NITROUS OXIDE, COMPRESSED - NON-FLAMMABLE GAS - 2 - OXIDIZER USP UN 1070

WARNING SECURE ALL CYLINDERS WHILE IN STORAGE AND IN USE.

CAUTION: FEDERAL LAW PROHIBITS DISPENSING WITHOUT A PRESCRIPTION

WARNING: ADMINISTRATION OF NITROUS OXIDE MAY BE HAZARDOUS OR CONTRAINDICATED. FOR USE ONLY BY OR UNDER THE SUPERVISION OF A LICENSED PRACTITIONER WHO IS EXPERIENCED IN THE USE AND ADMINISTRATION OF NITROUS OXIDE AND IS FAMILIAR WITH THE INDICATIONS, EFFECTS, DOSAGES, METHODS, AND FREQUENCY AND DURATION OF ADMINISTRATION, AND WITH THE HAZARDS CONTRAINDICATIONS AND SIDE EFFECTS AND THE PRECAUTIONS TO BE TAKEN.

GENERAL WARNINGS AND PRECAUTIONS

WARNING: HIGH PRESSURE OXIDIZING LIQUID AND GAS. VIGOROUSLY ACCELERATES COMBUSTION. CAN CAUSE RAPID SUFFOCATION. CAN CAUSE ANESTHETIC EFFECTS. MAY CAUSE FROSTBITE. AVOID BREATHING GAS. STORE AND USE WITH ADEQUATE VENTILATION. KEEP OIL AND GREASE AWAY. USE ONLY WITH EQUIPMENT CLEANED FOR NITROUS OXIDE AND RATED FOR CYLINDER PRESSURE. DO NOT GET LIQUID IN EYES ON SKIN OR CLOTHING. CYLINDER TEMPERATURE SHOULD NOT EXCEED 125 F (52 C) OPEN VALVE SLOWLY CLOSE VALVE AFTER EACH USE AND WHEN EMPTY. USE IN ACCORDANCE WITH THE MATERIAL SAFETY DATA SHEET (MSDS) NOTE: SUCK-BACK INTO CYLINDER MAY CAUSE RUPTURE. ALWAYS USE A BACK FLOW PREVENTATIVE DEVICE IN THE PIPING. FIRST AID: IF INHALED REMOVE TO FRESH AIR. IF NOT BREATHING GIVE ARTIFICIAL RESPIRATION. IF BREATHING DIFFICULT GIVE OXYGEN. CALL A PHYSICIAN. IN CASE OF FROSTBITE OBTAIN MEDICAL TREATMENT IMMEDIATELY.

DO NOT REMOVE THIS PRODUCT LABEL